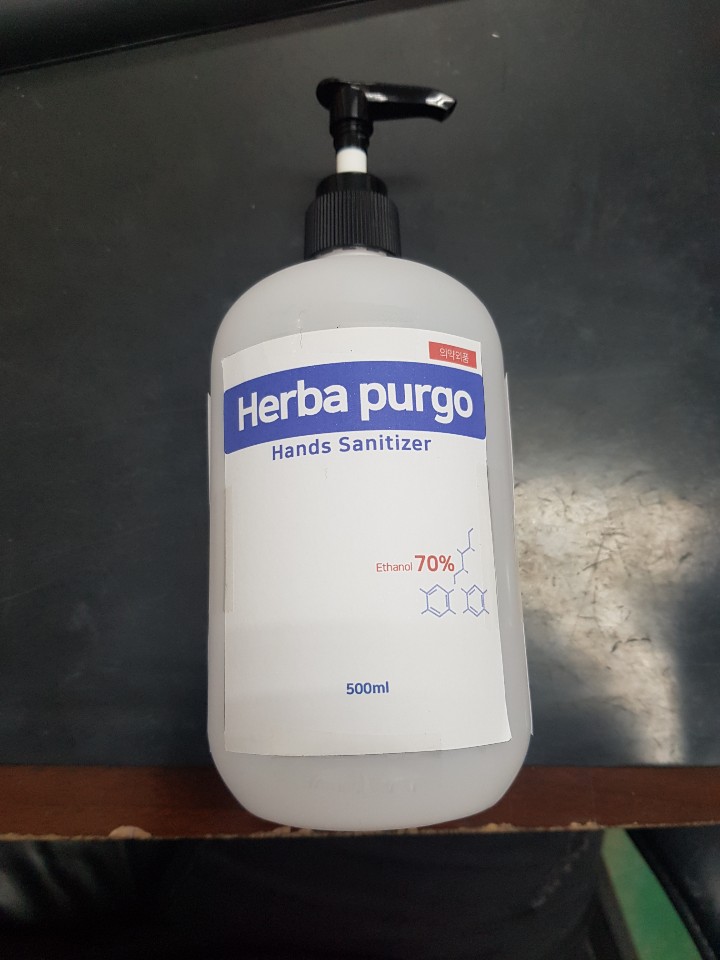 DRUG LABEL: Herba Purgo Hands Sanitizer Gel(Ethanol)
NDC: 73065-0006 | Form: GEL
Manufacturer: WOORILIFE&HEALTH
Category: otc | Type: HUMAN OTC DRUG LABEL
Date: 20200902

ACTIVE INGREDIENTS: ALCOHOL 350 mL/500 mL
INACTIVE INGREDIENTS: GLYCERIN; TROLAMINE; CARBOMER HOMOPOLYMER, UNSPECIFIED TYPE; ALOE VERA LEAF; PROPYLENE GLYCOL; CITRUS X LIMON FRUIT OIL; GREEN TEA LEAF; WATER

Woorilife&Health - Herba Purgo Hands Sanitizer Gel(Ethanol)

ACTIVE INGREDIENT

alcohol

INACTIVE INGREDIENT

glycerim, triethanolamine, carbomer, aloe barbadensis leaf extract, propylene glycol, citrus limon (lemon) fruit oil, green tea extract, hinoki oil, sage extract, calendula extract, water

PURPOSE

antiseptic

KEEP OUT OF REACH OF CHILDREN

Take moderate amount on hands and rub well to dry

INDICATIONS AND USAGE

- Adults and children 2 years of age and older

Brush teeth thoroughly preferably after each meal or at least twice a day or as directed by a dentist or docter.

- Children under 6 years

To minimize swallowing, use a pea-sized amount and supervise brushing until good habits are established.

- Children under 2 years

Consult a dentist or doctor

WARNINGS

1) Be careful not to swallow it, and rinse your mouth thoroughly after use.

2) If any abnormalities such as gum or mouth damage are caused by using this toothpaste, stop using the product and consult a doctor or dentist.

3) For children under 6 years of age, use a small amount of pea toothpaste per serving and use it under the supervision of a guardian to avoid sucking or swallowing.

4) If a child under 6 years of age swallows a large amount, consult a doctor or dentist immediately.

5) Keep out of reach of children under 6 years old.

DOSAGE AND ADMINISTRATION

for external use only